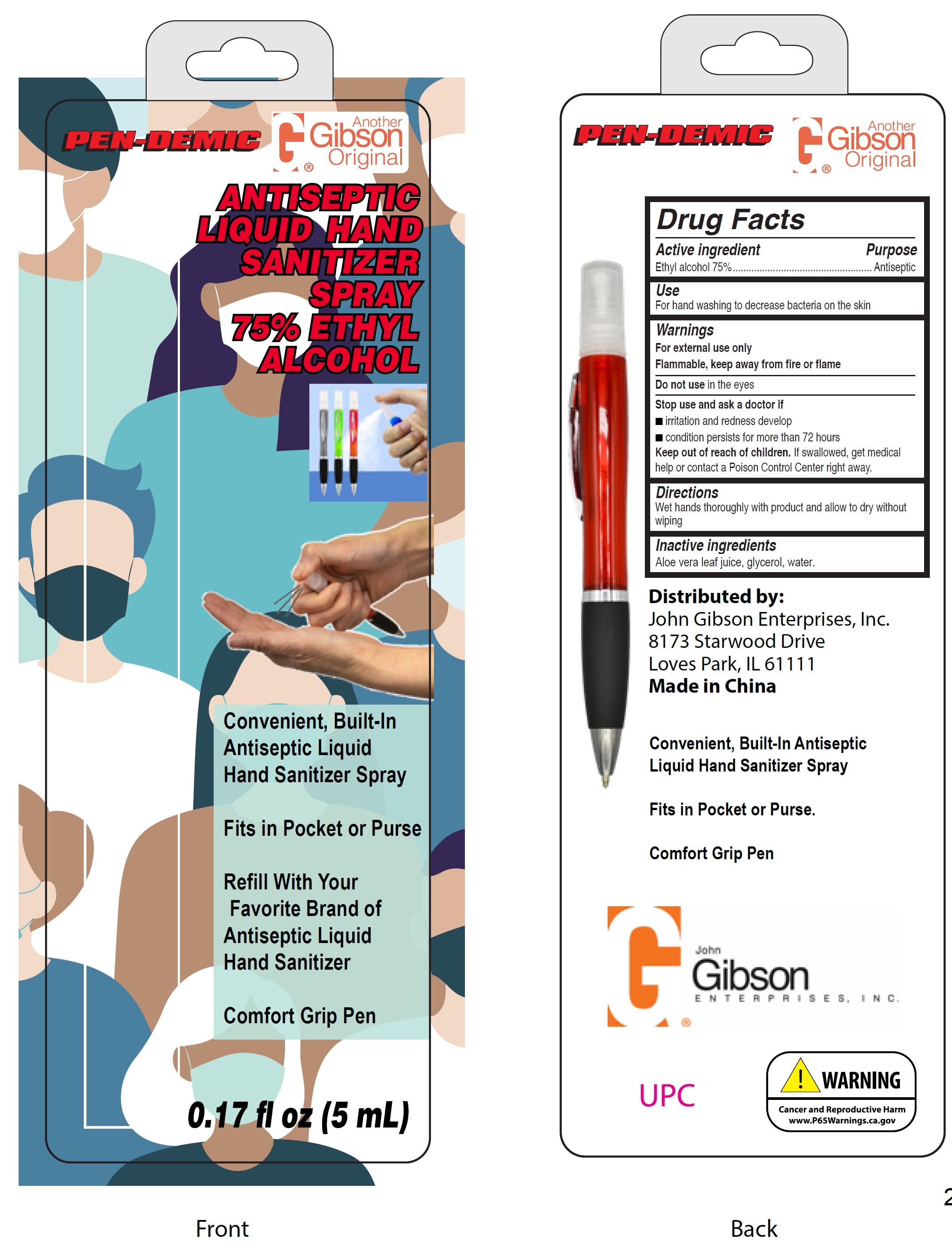 DRUG LABEL: Antiseptic Liquid Hand Sanitizer 75 Ethyl Alcohol
NDC: 81139-000 | Form: LIQUID
Manufacturer: John Gibson Enterprises, Inc.
Category: otc | Type: HUMAN OTC DRUG LABEL
Date: 20210112

ACTIVE INGREDIENTS: ALCOHOL 75 mL/100 mL
INACTIVE INGREDIENTS: ALOE VERA LEAF; GLYCERIN; WATER

Antiseptic Liquid Hand Sanitizer Spray 75% Ethyl Alcohol

Active ingredient

Ethyl alcohol 75%

Purpose

Antiseptic

Use

For hand washing to decrease bacteria on the skin

Warnings

For external use only
Flammable, keep away from fire or flame

Do not use

in the eyes

Stop use and ask a doctor if

- irritation and redness develop
- condition persists for more than 72 hours

Keep out of reach of children.

If swallowed, get medical help or contact a Poison Control Center right away.

Directions

Wet hands thoroughly with product and allow to dry without wiping

Inactive ingredients

Aloe vera leaf juice, glycerol, water.